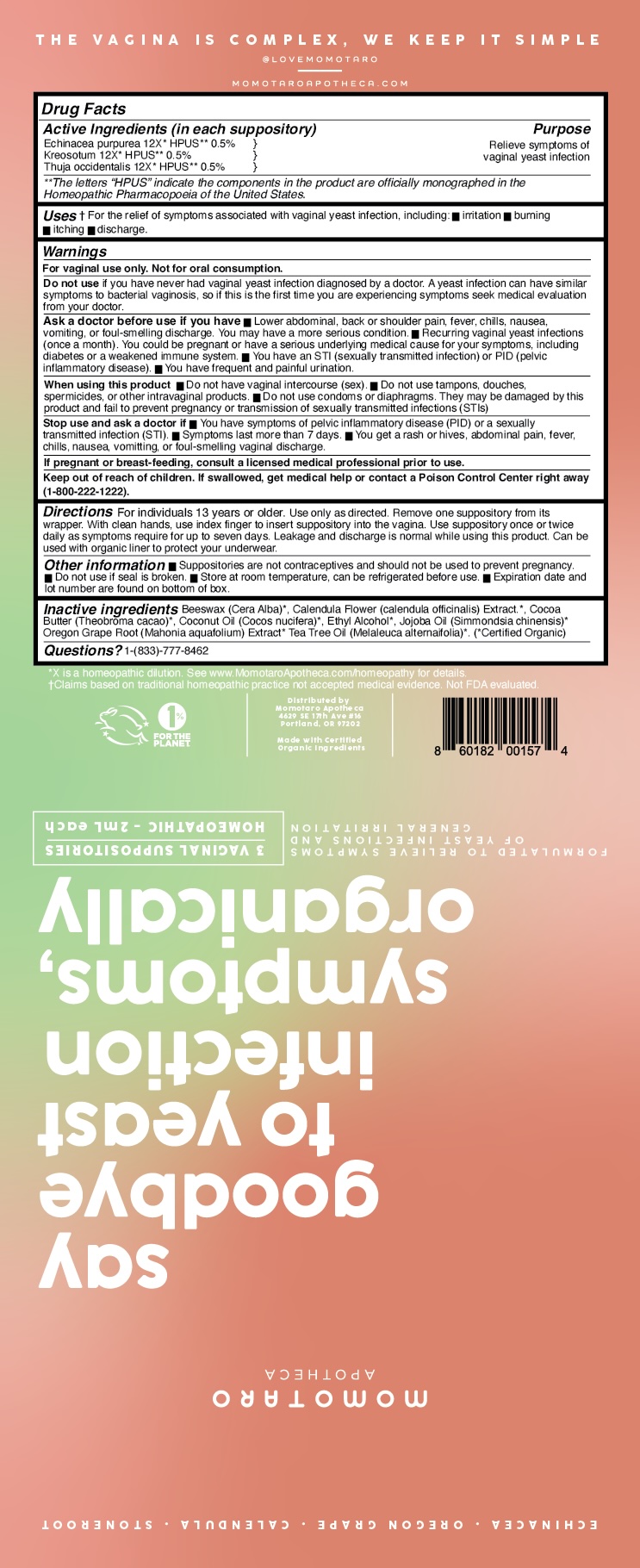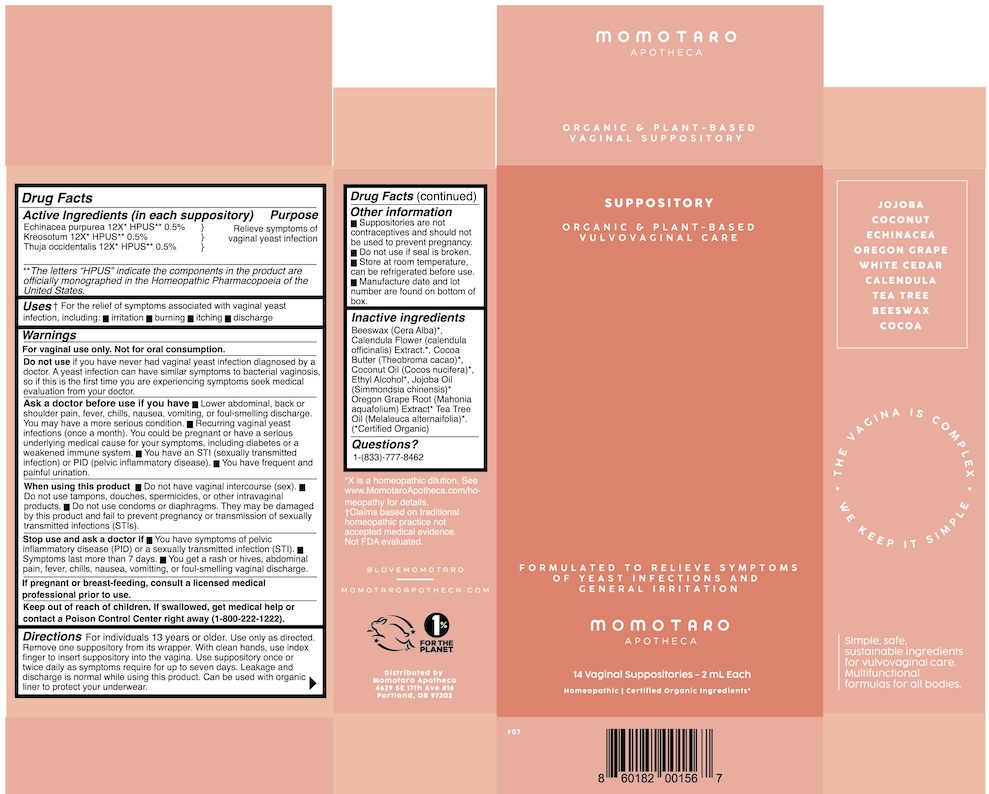 DRUG LABEL: ORGANIC AND PLANT-BASED VULVOVAGINAL CARE
NDC: 83385-001 | Form: SUPPOSITORY
Manufacturer: MOMOTARO APOTHECA LLC
Category: homeopathic | Type: HUMAN OTC DRUG LABEL
Date: 20250611

ACTIVE INGREDIENTS: ECHINACEA PURPUREA 12 [hp_X]/1 1; THUJA OCCIDENTALIS LEAFY TWIG 12 [hp_X]/1 1; WOOD CREOSOTE 12 [hp_X]/1 1
INACTIVE INGREDIENTS: JOJOBA OIL; BERBERIS AQUIFOLIUM ROOT BARK; BEESWAX; TEA TREE OIL; CALENDULA OFFICINALIS FLOWER; COCOA BUTTER; ALCOHOL

ORGANIC AND PLANT-BASED VULVOVAGINAL CARE

Active ingredients
Echinacea purpurea 12X HPUS
Kreosotum 12X HPUS
Thuja occidentalis 12X HPUS

Purpose

Relieve symptoms of vaginal yeast infection

Uses

For the relief of symptoms associated with vaginal yeast infection, including:

- irritation
- burning
- itching
- discharge.

Warnings

For vaginal use only. Not for oral consumption.

Stop use and ask a doctor if:

- You have symptoms of pelvic inflammatory disease (PID) or a sexually transmitted infection (STI)
- Symptoms last more than 7 days.
- • You get a rash or hives, abdominal pain, fever, chills, nausea, vomitting, or foul-smelling vaginal discharge.

PREGNANCY OR BREAST FEEDING

If pregnant or breast-feeding, consult a licensed medical professional prior to use.

Keep out of reach of children. If swallowed, get medical help or contact a Poison Control Center right away (1-800-222-1222).

Ask a doctor before use if you have

• Lower abdominal, back or shoulder pain, fever, chills, nausea, vomiting, or foul-smelling discharge. You may have a more serious condition. • Recurring vaginal yeast infections (once a month). You could be pregnant or have a serious underlying medical cause for your symptoms, including diabetes or a weakened immune system. • You have an STI (sexually transmitted infection) or PID (pelvic inflammatory disease).

• You have frequent and painful urination.

When using this product

- Do not have vaginal intercourse (sex).
- Do not use tampons, douches, spermicides, or other intravaginal products.
- Do not use condoms or diaphragms. They may be damaged by this product and fail to prevent pregnancy or transmission of sexually transmitted infections (STls)

Directions

Directions For individuals 13 years or older. Use only as directed. Remove one suppository from its wrapper. With clean hands, use index finger to insert suppository into the vagina. Use suppository once or twice daily as symptoms require for up to seven days. Leakage and discharge is normal while using this product. Can be used with organic liner to protect your underwear.

Other information

• Suppositories are not contraceptives and should not be used to prevent pregnancy.

• Do not use if seal is broken. • Store at room temperature, can be refrigerated before use. Expiration date and lot number are found on the bottom of the box

Inactive Ingredients

Beeswax (Cera Alba), Calendula Flower (calendula officinalis) Extract, Cocoa Butter (Theobroma cacao), Coconut Oil (Cocos nucifera), Ethyl Alcohol, Jojoba Oil (Simmondsia chinensis), Oregon Grape Root (Mahonia aquafolium) Extract, Tea Tree Oil (Melaleuca alternaifolia)".

Questions or comments?

1-(833)-777-8462

Do not use if you have never had vaginal yeast infection diagnosed by a doctor. A yeast infection can have similar symptoms to bacterial vaginosis, so if this is the first time you are experiencing symptoms seek medical evaluation from your doctor.